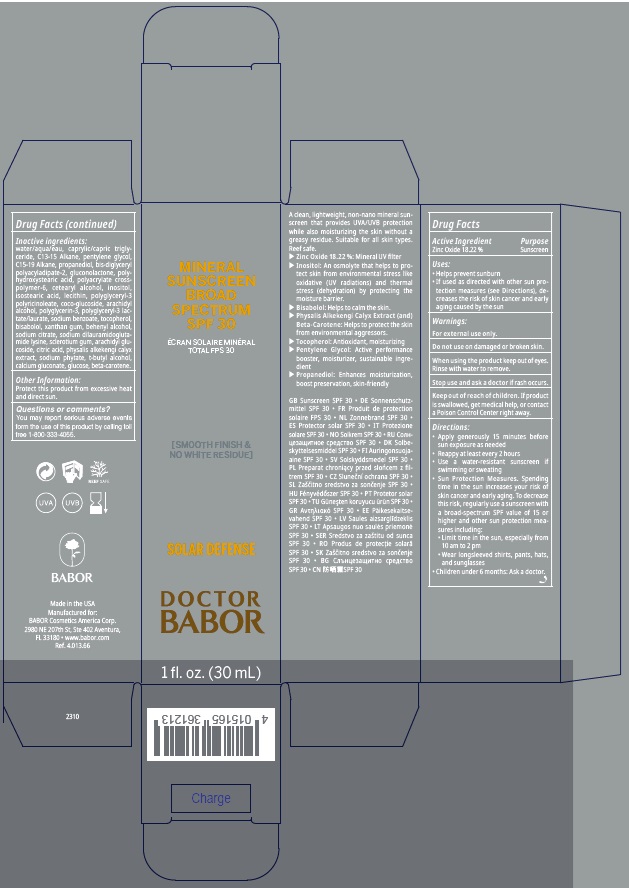 DRUG LABEL: DOCTOR BABOR SOLAR DEFENSE MINERAL SUNSCREEN BROAD SPECTRUM SPF 30
NDC: 44924-902 | Form: CREAM
Manufacturer: BABOR Cosmetics America Corp
Category: otc | Type: HUMAN OTC DRUG LABEL
Date: 20241212

ACTIVE INGREDIENTS: ZINC OXIDE 182.2 mg/1 mL
INACTIVE INGREDIENTS: POLYGLYCERIN-3; WATER; MEDIUM-CHAIN TRIGLYCERIDES; PROPANEDIOL; SODIUM CITRATE, UNSPECIFIED FORM; TERT-BUTYL ALCOHOL; INOSITOL; ISOSTEARIC ACID; LECITHIN, SOYBEAN; ARACHIDYL ALCOHOL; PHYTATE SODIUM; CALCIUM GLUCONATE; BETA CAROTENE; CITRIC ACID MONOHYDRATE; C15-19 ALKANE; TOCOPHEROL; GLUCONOLACTONE; AMMONIUM ACRYLOYLDIMETHYLTAURATE, DIMETHYLACRYLAMIDE, LAURYL METHACRYLATE AND LAURETH-4 METHACRYLATE COPOLYMER, TRIMETHYLOLPROPANE TRIACRYLATE CROSSLINKED (45000 MPA.S); CETOSTEARYL ALCOHOL; POLYGLYCERYL-3 PENTARICINOLEATE; COCO GLUCOSIDE; SODIUM BENZOATE; XANTHAN GUM; DOCOSANOL; BETASIZOFIRAN; ARACHIDYL GLUCOSIDE; PHYSALIS ALKEKENGI CALYX; ANHYDROUS DEXTROSE; SODIUM DILAURAMIDOGLUTAMIDE LYSINE; BIS-DIGLYCERYL POLYACYLADIPATE-2; POLYHYDROXYSTEARIC ACID (2300 MW); C13-15 ALKANE; PENTYLENE GLYCOL; LEVOMENOL

DOCTOR BABOR SOLAR DEFENSE MINERAL SUNSCREEN BROAD SPECTRUM SPF 30

Active Ingredient

Zinc Oxide 18.22%

Purpose

Sunscreen

Uses

- helps prevent sunburn
- if used as directed with other sun protection measures (see Directions), decreases the risk of skin cancer and early aging caused by the sun.

Warnings

For external use only.

Do not use

on damaged or broken skin.

When using the product

keep out of eyes. Rinse with water to remove.

Stop use and ask a doctor

if rash occurs.

Keep out of reach of children.

If product is swallowed, get medical help, or contact a Poison Control Center right away.

Directions

- Apply generously 15 minutes before sun exposure as needed.
- Reapply at least every 2 hours
- Use a water-resistant sunscreen if swimming or sweating
- Sun Protection Measures. Spending time in the sun increases your risk of skin cancer and early aging. To decrease this risk, regularly use a sunscreen with a broad-spectrum SPF value of 15 or higher and other sun protection measures including:
- Limit time in the sun, especially from 10 am to 2 pm
- Wear longsleeved shirts, pants, hats, and sunglasses
- Children under 6 months: Ask a doctor.

Inactive ingredients

water/aqua/eau, caprylic/capric triglyceride, C13-15 Alkane, pentylene glycol, C15-19 Alkane, propanediol, bis-diglyceryl polyacyladipate-2, gluconolactone, polyhydroxystearic acid, polyacrylate crosspolymer-6, cetearyl alcohol, inositol, isostearic acid, lecithin, polyglyceryl-3 polyricinoleate, coco-glucoside, arachidyl alcohol, polyglycerin-3, polyglyceryl-3 lactate/laurate, sodium benzoate, tocopherol, bisabolol, xanthan gum, behenyl alcohol, sodium citrate, sodium dilauramidoglutamide lysine, sclerotium gum, arachidyl glucoside, citric acid, physalis alkakengi calyx extract, sodium phytate, t-butyl alcohol, calcium gluconate, glucose, beta-carotene.

Other Information

Protect this product from excessive heat and direct sun

Questions or comments?

You may report serious adverse evenst from the use of this product by calling toll free 1-800-333-4055

Company Information

Made in the USA

Manufactured for:

BABOR Cosmetics America Corp.

2980 NE 207th St, Ste 402 Aventura,

FL 33180 www.babor.com